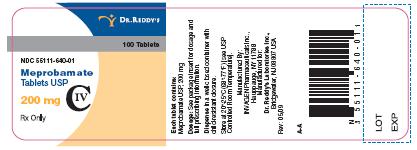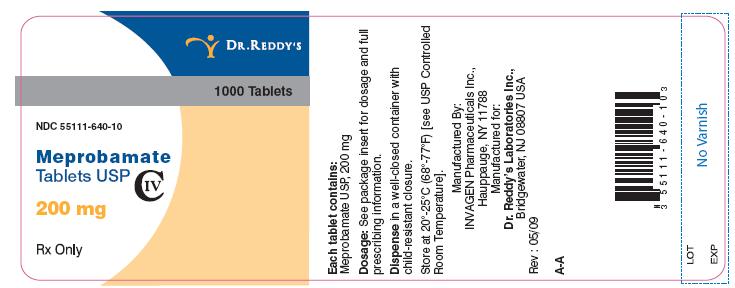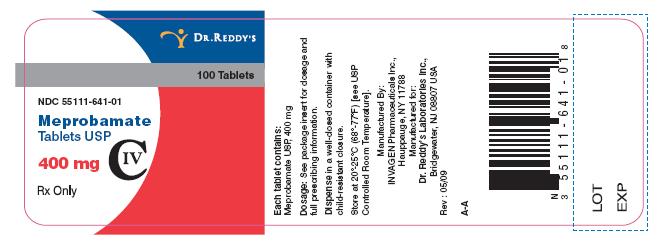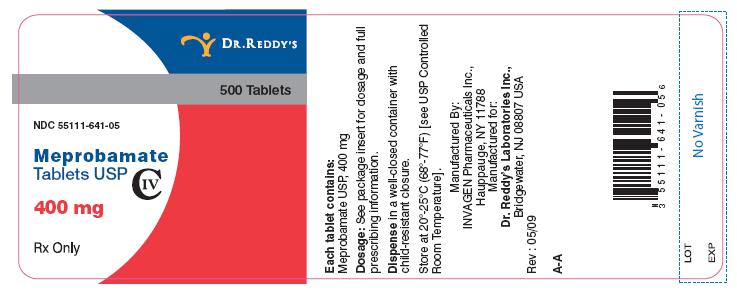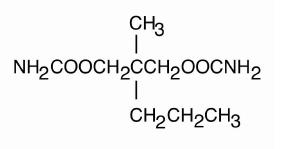 DRUG LABEL: Meprobamate
NDC: 55111-640 | Form: TABLET
Manufacturer: Dr.Reddy's Laboratories Limited
Category: prescription | Type: HUMAN PRESCRIPTION DRUG LABEL
Date: 20090909
DEA Schedule: CIV

ACTIVE INGREDIENTS: Meprobamate 200 mg/1 1
INACTIVE INGREDIENTS: cellulose, microcrystalline; starch, corn; colloidal silicon dioxide; stearic acid; magnesium stearate; sodium starch glycolate type A potato

Meprobamate Tablets

DESCRIPTION

Meprobamate is awhite powder with a characteristic odor and a bittertaste. It is slightly soluble in water, freely soluble in acetone andalcohol, and sparingly soluble in ether. The structural formula of meprobamate is:

C9H18N2O4 M.W.218.25

Meprobamate Tablets USP 200 mg and 400 mg for oral administrationcontain the following inactive ingredients: microcrystalline cellulose,sodium starch glycolate, pre-gelatinized starch, colloidal silicondioxide, stearic acid and magnesium stearate.

CLINICAL PHARMACOLOGY

Meprobamate is a carbamate derivative which has been shown inanimal studies to have effects at multiple sites in the central nervoussystem including the thalamus and limbic system.

INDICATIONS AND USAGE

Meprobamate tablets are indicated for the management of anxietydisorders or for the short-term relief of the symptoms of anxiety.Anxiety or tension associated with the stress of everyday life usuallydo not require treatment with an anxiolytic.

The effectiveness of meprobamate tablets in long-term use, that is,more than 4 months, has not been assessed by systematic clinicalstudies. The physician should periodically reassess the usefulness ofthe drug for the individual patient.

CONTRAINDICATIONS

Acute intermittent porphyria as well as allergic or idiosyncraticreactions to meprobamate or related compounds such ascarisoprodol, mebutamate, tybamate, or carbromal.

WARNINGS

Drug Dependence

Physical dependence, psychological dependence, and abuse haveoccurred. When chronic intoxication from prolonged use occurs, itusually involves ingestion of greater than recommended doses and ismanifested by ataxia, slurred speech, and vertigo. Therefore, carefulsupervision of dose and amounts prescribed is advised, as well asavoidance of prolonged administration, especially for alcoholics andother patients with a known propensity for taking excessive quantitiesof drugs.

Sudden withdrawal of the drug after prolonged and excessive use mayprecipitate recurrence of pre-existing symptoms such as anxiety,anorexia, insomnia, or withdrawal reactions such as vomiting, ataxia,tremors, muscle twitching, confusional states, hallucinosis, andrarely, convulsive seizures. Such seizures are more likely to occur inpersons with central nervous system damage or pre-existent or latentconvulsive disorders. Onset of withdrawal symptoms occurs usuallywithin 12 to 48 hours after discontinuation of meprobamate;symptoms usually cease within the next 12 to 48 hours.

When excessive dosage has continued for weeks or months, dosageshould be reduced gradually over a period of one or two weeks ratherthan abruptly stopped. Alternatively, a long-acting barbiturate may besubstituted, then gradually withdrawn.

Potentially Hazardous Tasks

Patients should be warned that meprobamate may impair the mentaland/or physical abilities required for performance of potentiallyhazardous tasks such as driving or operating machinery.

Additive Effects

Since the effects of meprobamate and alcohol or meprobamate andother CNS depressants or psychotropic drugs may be additive,appropriate caution should be exercised with patients who take morethan one of these agents simultaneously.

Usage in Pregnancy and Lactation

An increased risk of congenital malformations associated with theuse of minor tranquilizers (meprobamate, chlordiazepoxide anddiazepam) during the first trimester of pregnancy has beensuggested in several studies. Because use of these drugs is rarelya matter of urgency, their use during this period should almostalways be avoided. The possibility that a woman of childbearingpotential may be pregnant at the time of institution of therapyshould be considered. Patients should be advised that if they become pregnant during therapy or intend to become pregnant theyshould communicate with their physician about the desirability ofdiscontinuing the drug.

Meprobamate passes the placental barrier. It is present both inumbilical cord blood at or near maternal plasma levels and inbreast milk of lactating mothers at concentrations two to four timesthat of maternal plasma. When use of meprobamate iscontemplated in breastfeeding patients, the drug's higherconcentration in breast milk as compared to maternal plasmashould be considered.

Usage in Children

Meprobamate tablets should not be administered to children underage six, since there is a lack of documented evidence for safety andeffectiveness in this age group.

PRECAUTIONS

The lowest effective dose should be administered, particularly toelderly and/or debilitated patients, in order to preclude oversedation.

The possibility of suicide attempts should be considered and the leastamount of drug feasible should be dispensed at anyone time.

Meprobamate is metabolized in the liver and excreted by the kidney; toavoid its excess accumulation, caution should be exercised inadministration to patients with compromised liver or kidney function.

Meprobamate occasionally may precipitate seizures in epilepticpatients.

Geriatric Use

Clinical studies of meprobamate tablets did not include sufficientnumbers of subjects aged 65 and over to determine whether theyrespond differently from younger subjects. Other reported clinicalexperience has not identified differences in responses between theelderly and younger patients. In general, dose selection for an elderlypatient should be cautious, usually starting at the low end of thedosing range, reflecting the greater frequency of decreased hepatic,renal, or cardiac function, and of concomitant disease or other drug therapy.

ADVERSE REACTIONS

Central Nervous System

Drowsiness, ataxia, dizziness, slurred speech, headache, vertigo,weakness, paresthesias, impairment of visual accommodation,euphoria, overstimulation, paradoxical excitement, fast EEG activity.

Gastrointestinal

Nausea, vomiting, diarrhea.

Cardiovascular

Palpitation, tachycardia, various forms of arrhythmia, transient ECGchanges, syncope; also hypotensive crisis (including one fatal case).

Allergic or idiosyncratic reactions are usually seen within the period ofthe first to fourth dose in patients having had no previous contact withthe drug. Milder reactions are characterized by an itchy, urticarial, orerythematous maculopapular rash which may be generalized orconfined to the groin. Other reactions have included leukopenia, acutenonthrombocytopenic purpura, petechiae, ecchymoses, eosinophilia,peripheral edema, adenopathy, fever, fixed drug eruption with crossreaction to carisoprodol, and cross sensitivity betweenmeprobamate/mebutamate and meprobamate/carbromal.

More severe hypersensitivity reactions, rarely reported, includehyperpyrexia, chills, angioneurotic edema, bronchospasm, oliguriaand anuria. Also, anaphylaxis, erythema multiforme, exfoliativedermatitis, stomatitis, proctitis, Stevens-Johnson syndrome andbullous dermatitis, including one fatal case of the latter followingadministration of meprobamate in combination with prednisolone.

In case of allergic or idiosyncratic reactions to meprobamate,discontinue the drug and initiate appropriate symptomatic therapy,which may include epinephrine, antihistamines, and in severe cases,corticosteroids. In evaluating possible allergic reactions, also considerallergy to excipients.

Hematologic

(See also Allergic or Idiosyncratic). Agranulocytosis and aplasticanemia have been reported. These cases rarely were fatal. Rare casesof thrombocytopenic purpura have been reported.

Other

Exacerbation of porphyric symptoms.

OVERDOSAGE

Suicidal attempts with meprobamate have resulted in drowsiness,lethargy, stupor, ataxia, coma, shock, vasomotor, and respiratorycollapse. Some suicidal attempts have been fatal.

The following data on meprobamate tablets have been reported in theliterature and from other sources. These data are not expected tocorrelate with each case (considering factors such as individual susceptibility and length of time from ingestion to treatment), butrepresent the usual ranges reported.

Acute simple overdose

(meprobamate alone): Death has beenreported with ingestion of as little as 12 g meprobamate and survivalwith as much as 40 g.

Blood levels

0.5-2 mg% represents the usual blood level range of meprobamateafter therapeutic doses. The level may occasionally be as high as 3mg%.

3-10 mg% usually corresponds to findings of mild to moderatesymptoms of overdosage, such as stupor or light coma.

10-20 mg% usually corresponds to deeper coma, requiring moreintensive treatment. Some fatalities occur.

At levels greater than 20 mg%, more fatalities than survivals can beexpected.

Acute combined overdose

(meprobamate with alcohol or other CNSdepressants or psychotropic drugs): Since effects can be additive, ahistory of ingestion of a low dose of meprobamate plus any of thesecompounds (or of a relative low blood or tissue level) cannot be usedas a prognostic indicator.

In cases where excessive doses have been taken, sleep ensues rapidlyand blood pressure, pulse, and respiratory rates are reduced to basallevels. Any drug remaining in the stomach should be removed andsymptomatic therapy given. Should respiration or blood pressurebecome compromised, respiratory assistance, central nervous systemstimulants, and pressor agents should be administered cautiously asindicated. Meprobamate is metabolized in the liver and excreted by thekidney. Diuresis, osmotic (mannitol) diuresis, peritoneal dialysis, andhemodialysis have been used successfully. Careful monitoring ofurinary output is necessary and caution should be taken to avoidoverhydration. Relapse and death, after initial recovery, have beenattributed to incomplete gastric emptying and delayed absorption.Meprobamate can be measured in biological fluids by two methods:colorimetric (Hoffman, A.J. and Ludwig, B.J.: J Amer Pharm Assn 48:740, 1959) and gas chromatographic (Douglas, J.F. et al: Anal Chern39: 956, 1967).

DOSAGE AND ADMINISTRATION

Meprobamate Tablets USP: The usual adult daily dosage is 1200 mgto 1600 mg, in three or four divided doses; adaily dosage above 2400mg is not recommended. The usual daily dosage for children ages sixto twelve years is 200 mg to 600 mg, in two or three divided doses.

Not recommended for children under age 6 (see Usage in Children).

HOW SUPPLIED

Meprobamate Tablets USP 200 mg are white, round, biconvex tabletsdebossed with I and 7 on one side and bisect on the other.

Supplied in bottles of 100 and 1000.

Bottles of 100: NDC 55111-640-01

Bottles of 1000: NDC 55111-640-10

Meprobamate Tablets USP 400 mg are white, round, biconvex tabletsdebossed with I and 4 on one side and bisect on the other.

Supplied in bottles of 100 and 500.

Bottles of 100: NDC 55111-641-01

Bottles of 500: NDC 55111-641-05

Dispense in well-closed container with child-resistant closure.

Store at 20°-25°C (68°-77°F) [see USP Controlled RoomTemperature].

Manufactu red by:

InvaGen Pharmaceuticals, Inc

Hauppauge, NY 11788

Manufactured for:

Dr. Reddy's Laboratories Inc.,

Bridgewater, NJ 08807 USA

Rev: 05/09

200 mg - CONTAINER LABELS

100's count

1000's count

400 mg - CONTAINER LABELS

100's count

500's count